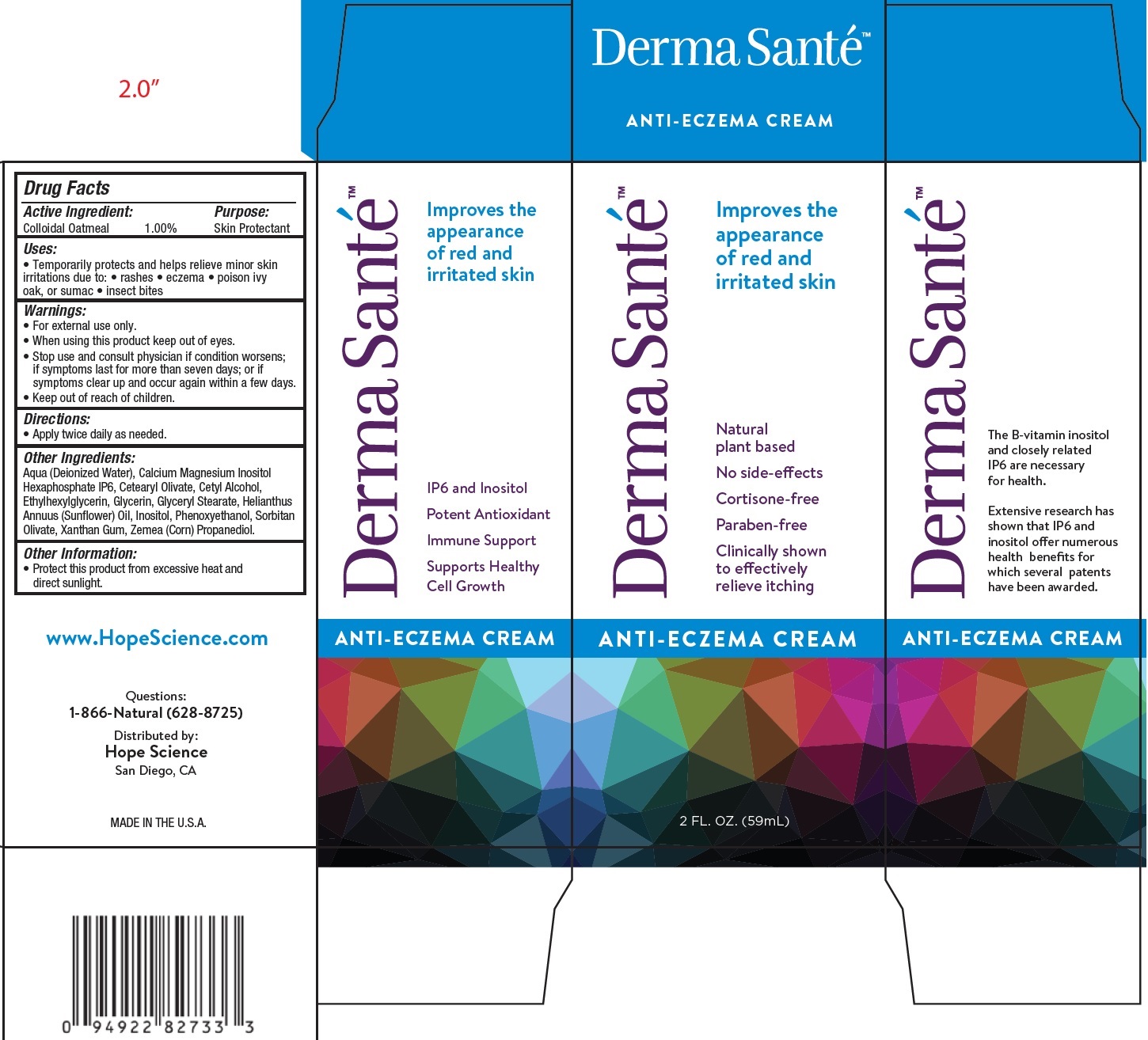 DRUG LABEL: DERMA SANTE Anti Eczema Cream
NDC: 71970-324 | Form: CREAM
Manufacturer: Hope Science Inc.
Category: otc | Type: HUMAN OTC DRUG LABEL
Date: 20231111

ACTIVE INGREDIENTS: OATMEAL 10 mg/1 mL
INACTIVE INGREDIENTS: WATER; CETEARYL OLIVATE; CETYL ALCOHOL; ETHYLHEXYLGLYCERIN; GLYCERIN; GLYCERYL MONOSTEARATE; HELIANTHUS ANNUUS FLOWERING TOP; INOSITOL; PHENOXYETHANOL; SORBITAN OLIVATE; XANTHAN GUM; CORN; PROPANEDIOL

DERMA SANTE' Anti Eczema Cream

Active Ingredient:

Colloidal Oatmeal 1.00%

Purpose:

Skin Protectant

Uses:

• Temporarily protects and helps relieve minor skin irritations due to: • rashes • eczema • poison ivy oak, or sumac • insect bites

Warnings:

• For external use only.

When using this product

- keep out of eyes.

undefined

- physician if condition worsens; if symptoms last for more than seven days; or if symptoms clear up and occur again within a few days.

Directions:

• Apply twice daily as needed.

Other Ingredients:

Aqua (Deionized Water), Calcium Magnesium Inositol Hexaphosphate IP6, Cetearyl Olivate, Cetyl Alcohol, Ethylhexylglycerin, Glycerin, Glyceryl Stearate, Helianthus Annuus (Sunflower) Oil, Inositol, Phenoxyethanol, Sorbitan Olivate, Xanthan Gum, Zemea (Corn) Propanediol.

Other Information:

• Protect this product from excessive heat and direct sunlight.